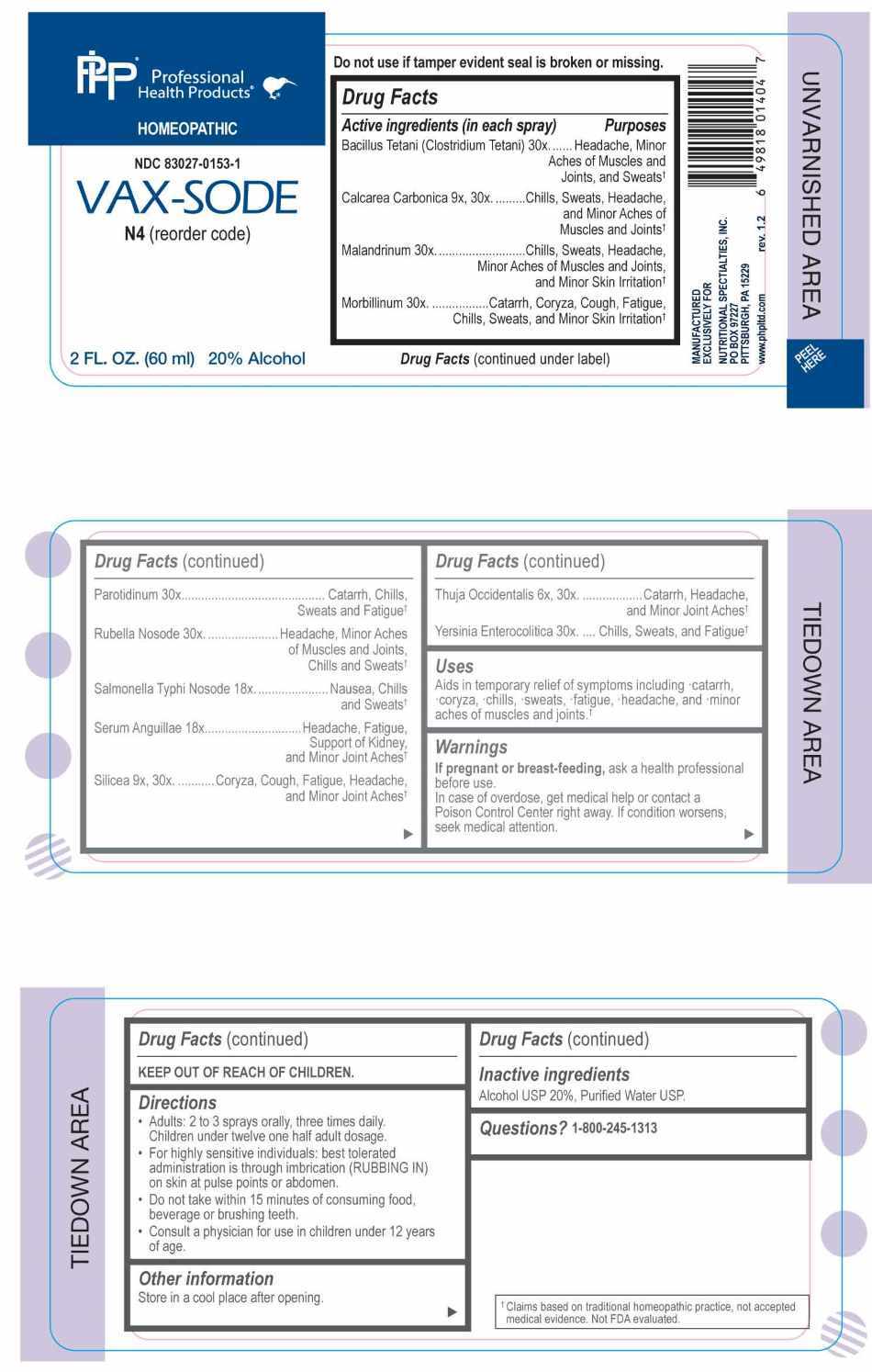 DRUG LABEL: Vax-Sode
NDC: 83027-0153 | Form: SPRAY
Manufacturer: Nutritional Specialties, Inc.
Category: homeopathic | Type: HUMAN OTC DRUG LABEL
Date: 20250922

ACTIVE INGREDIENTS: THUJA OCCIDENTALIS LEAFY TWIG 6 [hp_X]/1 mL; OYSTER SHELL CALCIUM CARBONATE, CRUDE 9 [hp_X]/1 mL; SILICON DIOXIDE 9 [hp_X]/1 mL; SALMONELLA ENTERICA ENTERICA SEROVAR TYPHI 18 [hp_X]/1 mL; ANGUILLA ROSTRATA BLOOD SERUM 18 [hp_X]/1 mL; CLOSTRIDIUM TETANI 30 [hp_X]/1 mL; VACCINIA VIRUS 30 [hp_X]/1 mL; MEASLES VIRUS 30 [hp_X]/1 mL; MUMPS VIRUS 30 [hp_X]/1 mL; RUBELLA VIRUS 30 [hp_X]/1 mL; YERSINIA ENTEROCOLITICA 30 [hp_X]/1 mL
INACTIVE INGREDIENTS: WATER; ALCOHOL

DRUG FACTS:

ACTIVE INGREDIENTS:

Bacillus Tetani (Clostridium Tetani) 30X, Calcarea Carbonica 9X, 30X , Malandrinum 30X, Morbillinum 30X, Parotidinum 30X, Rubella Nosode 30X, Salmonella Typhi Nosode 18X, Serum Anguillae 18X, Silicea 9X, 30X, Thuja Occidentalis 6X, 30X, Yersinia Enterocolitica 30X.

PURPOSE:

Bacillus Tetani (Clostridium Tetani) – Headache, Minor Aches of Muscles and Joints, and Sweats,† Calcarea Carbonica – Chills, Sweats, Headache, and Minor Aches of Muscles and Joints,† Malandrinum – Chills, Sweats, Headache, Minor Aches of Muscles and Joints, and Minor Skin Irritation,† Morbillinum – Catarrh, Coryza, Cough, Fatigue, Chills, Sweats, and Minor Skin Irritation,† Parotidinum – Catarrh, Chills, Sweats and Fatigue,† Rubella Nosode – Headache, Minor Aches of Muscles and Joints, Chills and Sweats,† Salmonella Typhi Nosode – Nausea, Chills and Sweats,† Serum Anguillae – Headache, Fatigue, Support of Kidney, and Minor Joint Aches,† Silicea – Coryza, Cough, Fatigue, Headache, and Minor Joint Aches,† Thuja Occidentalis – Catarrh, Headache, and Minor Joint Aches,† Yersinia Enterocolitica – Chills, Sweats, and Fatigue†

†Claims based on traditional homeopathic practice, not accepted medical evidence. Not FDA evaluated.

USES:

Aids in temporary relief of symptoms including catarrh, coryza, chills, sweats, fatigue, headache, and minor aches of muscles and joints.†

†Claims based on traditional homeopathic practice, not accepted medical evidence. Not FDA evaluated.

WARNINGS:

If pregnant or breast-feeding, ask a health professional before use.

In case of overdose, get medical help or contact a Poison Control Center right away.

If condition worsens, seek medical attention.

KEEP OUT OF REACH OF CHILDREN

Do not use if tamper evident seal is broken or missing.

Store in a cool place after opening

KEEP OUT OF REACH OF CHILDREN:

In case of overdose, get medical help or contact a Poison Control Center right away.

DIRECTIONS:

• Adults: 2 to 3 sprays orally, three times daily. Children under twelve one half adult dosage.

• For highly sensitive individuals: best tolerated administration is through imbrication (RUBBING IN) on skin at pulse points or abdomen.

• Do not take within 15 minutes of consuming food, beverage or brushing teeth.

• Consult a physician for use in children under 12 years of age.

INACTIVE INGREDIENTS:

Alcohol USP 20%, Purified Water USP.

QUESTIONS:

MANUFACTURED EXCLUSIVELY FOR

NUTRITIONAL SPECIALTIES, INC.

PO BOX 97227

PITTSBURGH, PA 15229

www.phpitd.com

1-800-245-1313

PACKAGE LABEL DISPLAY:

Professional Health Products

HOMEOPATHIC

NDC 83027-0153-1

VAX-SODE

2 FL. OZ. (60ml)